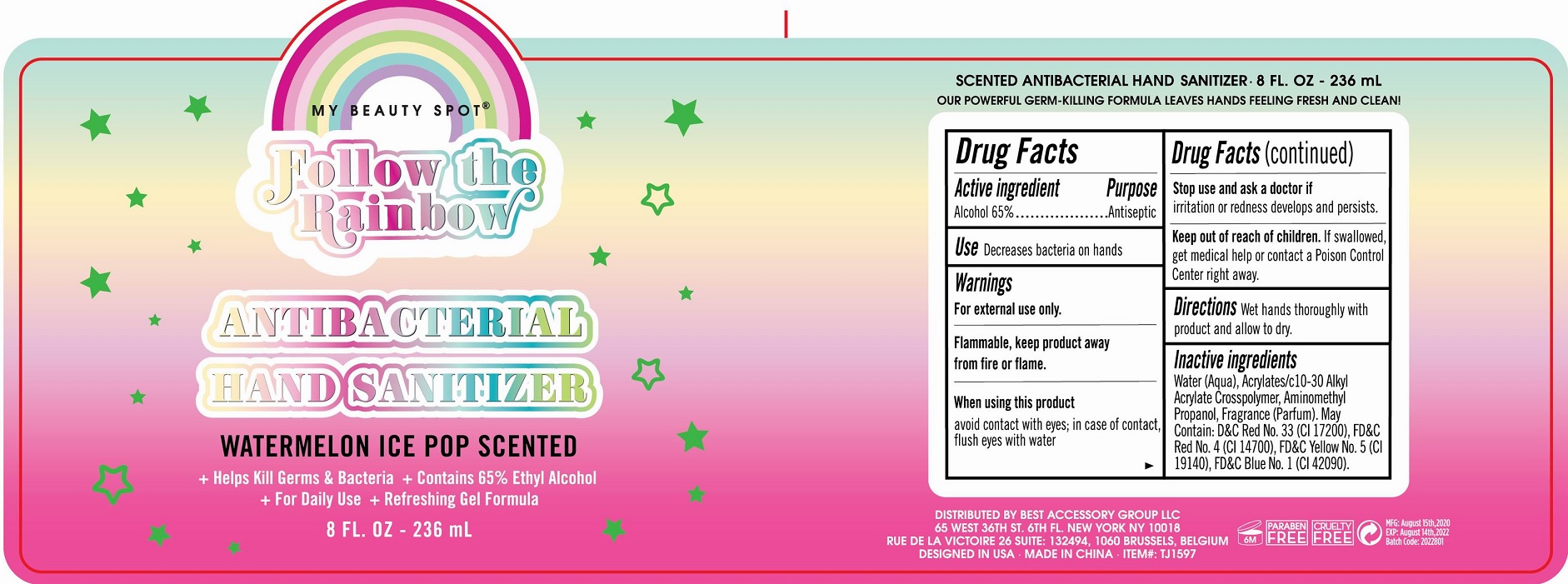 DRUG LABEL: Follow the Rainbow Antibacterial Hand Sanitizer Watermelon Ice Pop scented
NDC: 56136-089 | Form: GEL
Manufacturer: Ganzhou Olivee Cosmetic Co., Ltd.
Category: otc | Type: HUMAN OTC DRUG LABEL
Date: 20200730

ACTIVE INGREDIENTS: ALCOHOL 65 mL/100 mL
INACTIVE INGREDIENTS: water; CARBOMER COPOLYMER TYPE A; AMINOMETHYLPROPANOL; GLYCERIN; FD&C RED NO. 4; FD&C BLUE NO. 1; FD&C YELLOW NO. 5; D&C RED NO. 33

hand sanitizer

Active ingredient

Alcohol 65%

Purpose

Antiseptic

USE

Decrease bacteria on hands

Warnings

For external use only.

When using this product

avoid contact with eyes; in case of contact, flush eyes with water.

Stop use and ask a doctor if

- irritation and redness develops and persists.

Keep out of reach of children.

If swallowed, get medical help or contact a Poison Control Center right away.

Directions

Wet hands thoroughly with product and allow to dry.

Inactive ingredients

Water (Aqua), Acrylates/c 10-30 Alkyl Acrylate Crosspolymer, Aminomethyl Propanol, Fragrace (Parfum). May contain: FD&C No. 4 (C.l. 14700), D&C Red No. 33 (Cl 17200), FD&C Yellow 5, FD&C Blue No. 1 (Cl 42090).